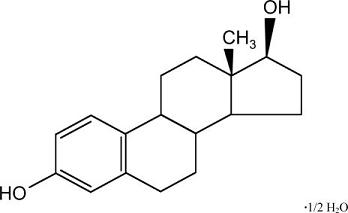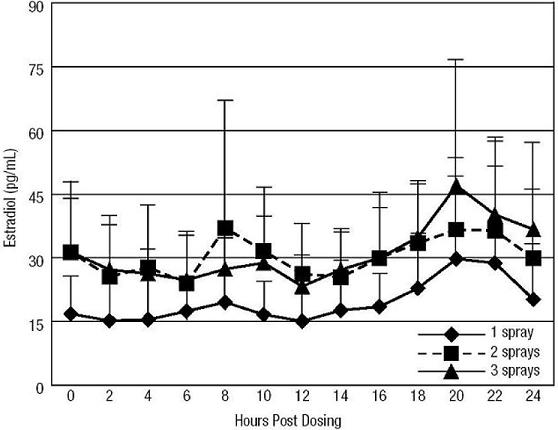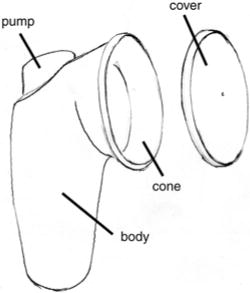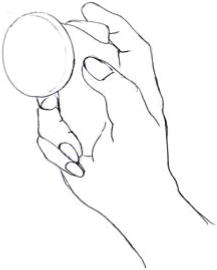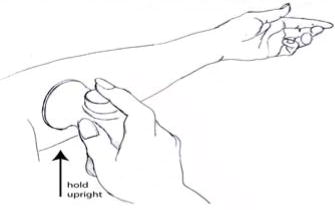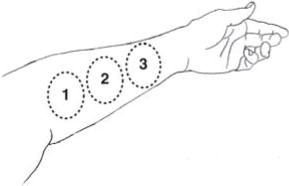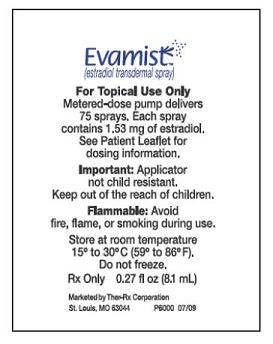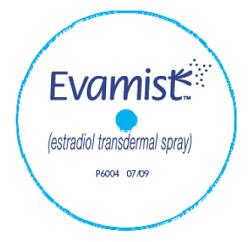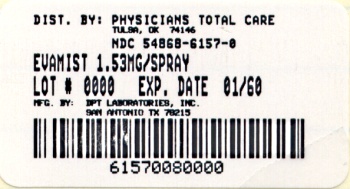 DRUG LABEL: Evamist
NDC: 54868-6157 | Form: SPRAY, METERED
Manufacturer: Physicians Total Care, Inc.
Category: prescription | Type: HUMAN PRESCRIPTION DRUG LABEL
Date: 20100824

ACTIVE INGREDIENTS: ESTRADIOL 1.53 mg/1 1
INACTIVE INGREDIENTS: OCTISALATE; ALCOHOL

HIGHLIGHTS OF PRESCRIBING INFORMATION

These highlights do not include all the information needed to use Evamist safely and effectively. See full prescribing information for Evamist. Evamist (estradiol transdermal spray) Initial U.S. Approval: 1975

WARNING: ENDOMETRIAL CANCER, CARDIOVASCULAR DISORDERS, BREAST CANCER, AND PROBABLE DEMENTIA

See full prescribing information for complete boxed warning.

- There is an increased risk of endometrial cancer in women with a uterus who use unopposed estrogens (5.2)
- Women's Health Initiative substudies reported increased risks of stroke, deep vein thrombosis, pulmonary embolism, invasive breast cancer, myocardial infarction, and probable dementia (14.4, 14.5)
- Estrogens with or without progestins should not be used for the prevention of cardiovascular disease or dementia (5.1, 5.3)
- Use estrogens with or without progestins at the lowest dose and for the shortest duration consistent with treatment goals and individual risks (2)

1 INDICATIONS AND USAGE

Evamist is an estrogen indicated for the treatment of moderate to severe vasomotor symptoms due to menopause (1)

2 DOSAGE AND ADMINISTRATION

- One spray once daily to forearm as a starting dose (2.2)
- Increase to two or three sprays daily to forearm based upon clinical response (2.2)

3 DOSAGE FORMS AND STRENGTHS

- One spray delivers 90 mcL that contains 1.53 mg estradiol

4 CONTRAINDICATIONS

- Undiagnosed abnormal genital bleeding (4)
- Known, suspected, or history of cancer of the breast (4, 5.2)
- Known or suspected estrogen-dependent neoplasia (4, 5.2)
- Active deep vein thrombosis, pulmonary embolism, or history of these conditions (4, 5.1)
- Active or recent (within the past year) arterial thromboembolic disease (for example, stroke and myocardial infarction) (4, 5.1)
- Known liver dysfunction or disease (4, 5.9)
- Known or suspected pregnancy (4, 8.1)

5 WARNINGS AND PRECAUTIONS

- An increased risk of stroke, deep vein thrombosis, pulmonary embolism, myocardial infarction, and probable dementia has been reported with the use of estrogens with or without progestins (5.1, 5.3)
- An increased risk of invasive breast cancer has been reported with the use of estrogens plus progestins (5.2)
- Estrogens increase the risk of gallbladder disease (5.4)
- Discontinue estrogens if severe hypercalcemia, loss of vision, severe hypertriglyceridemia or cholestatic jaundice occurs (5.5, 5.6, 5.9, 5.10)
- Monitor thyroid function in women on thyroid hormone replacement therapy (5.11, 5.19)

6 ADVERSE REACTIONS

Most common adverse reactions (≥5%) are: headache, breast tenderness and nipple pain, nausea, back pain, and nasopharyngitis (6.1)

To report SUSPECTED ADVERSE REACTIONS, contact Ther-Rx Corporation at 1-877-567-7676 or FDA at 1-800-FDA-1088 or www.fda.gov/medwatch.

7 DRUG INTERACTIONS

- Estrogen products may interact with inducers and inhibitors of CYP3A4 (7.1)

8 USE IN SPECIFIC POPULATIONS

- Nursing Mothers: Estrogen administration to nursing mothers has been shown to decrease the quantity and quality of the breast milk (8.3)
- Geriatric Use: An increased risk of probable dementia in women over 70 years of age was reported in the two substudies of the Women's Health Initiative Memory Study (8.5)

FULL PRESCRIBING INFORMATION

WARNING -- ENDOMETRIAL CANCER, CARDIOVASCULAR AND OTHER RISKS

ENDOMETRIAL CANCER

Adequate diagnostic measures, including endometrial sampling when indicated, should be undertaken to rule out malignancy in all cases of undiagnosed persistent or recurring abnormal vaginal bleeding [see Warnings and Precautions (5.2)].

CARDIOVASCULAR AND OTHER RISKS

Estrogens with or without progestins should not be used for the prevention of cardiovascular disease or dementia [see Warnings and Precautions (5.1) and (5.3) and Clinical Studies (14.4 and 14.5)].

The Women's Health Initiative (WHI) estrogen alone substudy reported increased risks of stroke and deep vein thrombosis (DVT) in postmenopausal women (50 to 79 years of age) during 6.8 years and 7.1 years, respectively, of treatment with daily oral conjugated estrogens (CE 0.625 mg), relative to placebo [see Warnings and Precautions (5.1) and Clinical Studies (14.4)].

The estrogen plus progestin WHI substudy reported increased risk of myocardial infarction, stroke, invasive breast cancer, pulmonary emboli, and DVT in postmenopausal women (50 to 79 years of age) during 5.6 years of treatment with daily oral CE 0.625 mg combined with medroxyprogesterone acetate (MPA 2.5 mg), relative to placebo [see Warnings and Precautions (5.1) and (5.2) and Clinical Studies (14.4)].

The Women's Health Initiative Memory Study (WHIMS), a substudy of the WHI, reported increased risk of developing probable dementia in postmenopausal women 65 years of age or older during 5.2 years of treatment with daily CE 0.625 mg alone and during 4 years of treatment with daily CE 0.625 mg combined with MPA 2.5 mg, relative to placebo. It is unknown whether this finding applies to younger postmenopausal women [see Warnings and Precautions (5.3), Use in Specific Populations (8.5) and Clinical Studies (14.5)].

In the absence of comparable data, these risks should be assumed to be similar for other doses of CE and MPA and other combinations and dosage forms of estrogens and progestins. Because of these risks, estrogens with or without progestins should be prescribed at the lowest effective doses and for the shortest duration consistent with treatment goals and risks for the individual woman.

1 INDICATIONS AND USAGE

Evamist (estradiol transdermal spray) is an estrogen indicated for the treatment of moderate to severe vasomotor symptoms due to menopause.

2 DOSAGE AND ADMINISTRATION

Enter section text here

2.1 General Dosing Information

When estrogen is prescribed for a postmenopausal woman with a uterus, generally, a progestin should also be initiated to reduce the risk of endometrial cancer. A woman without a uterus does not need progestin.

Use of estrogen, alone or in combination with a progestin, should be with the lowest effective dose and for the shortest duration consistent with treatment goals and risks for the individual woman. Postmenopausal women should be re-evaluated periodically as clinically appropriate (for example at 3-month to 6-month intervals) to determine if treatment is still necessary.

2.2 Treatment of Moderate to Severe Vasomotor Symptoms

Evamist therapy should be initiated with one spray per day. Dosage adjustment should be guided by the clinical response.

Before applying the first dose from a new applicator, the pump should be primed by spraying 3 sprays with the cover on. The container should be held upright and vertical for spraying.

One, two or three sprays are applied each morning to adjacent, non-overlapping areas on the inner surface of the forearm, starting near the elbow. Sprays should be allowed to dry for approximately 2 minutes and the site should not be washed for 30 minutes. Application of Evamist to other skin surfaces has not been adequately studied. Evamist should not be applied to skin surfaces other than the forearm.

3 DOSAGE FORMS AND STRENGTHS

Evamist is an estradiol transdermal spray. One spray delivers 90 mcL that contains 1.53 mg of estradiol.

4 CONTRAINDICATIONS

Evamist should not be used in women with any of the following conditions:

- Undiagnosed abnormal genital bleeding
- Known, suspected, or history of cancer of the breast
- Known or suspected estrogen-dependent neoplasia
- Active deep vein thrombosis, pulmonary embolism, or history of these conditions
- Active or recent (within the past year) arterial thromboembolic disease (for example, stroke and myocardial infarction)
- Known liver dysfunction or disease
- Known or suspected pregnancy

5 WARNINGS AND PRECAUTIONS

Enter section text here

5.1 Cardiovascular Disorders

An increased risk of stroke and deep vein thrombosis (DVT) has been reported with estrogen alone therapy. An increased risk of stroke, DVT, pulmonary embolism, and myocardial infarction has been reported with estrogen plus progestin therapy. Should any of these occur or be suspected, estrogens with or without progestins should be discontinued immediately.

Risk factors for arterial vascular disease (for example, hypertension, diabetes mellitus, tobacco use, hypercholesterolemia, and obesity) and/or venous thromboembolism (for example, personal history or family history of venous thromboembolism [VTE], obesity, and systemic lupus erythematosus) should be managed appropriately.

Stroke

In the Women's Health Initiative (WHI) estrogen alone substudy, a statistically significant increased risk of stroke was reported in women receiving daily conjugated estrogens (CE 0.625 mg) compared to placebo (45 versus 33 per 10,000 women-years). The increase in risk was demonstrated in year 1 and persisted^1 [see Clinical Studies (14.4)].

In the estrogen plus progestin substudy of WHI, a statistically significant increased risk of stroke was reported in women receiving daily CE 0.625 mg plus medroxyprogesterone acetate (MPA 2.5 mg) compared to placebo (31 versus 24 per 10,000 women-years). The increase in risk was demonstrated after the first year and persisted [see Clinical Studies (14.4)].

Coronary heart disease

In the estrogen alone substudy of WHI, no overall effect on coronary heart disease (CHD) events (defined as non-fatal myocardial infarction [MI], silent MI, or CHD death) was reported in women receiving estrogen alone compared to placebo^2 [see Clinical Studies (14.4)].

In the estrogen plus progestin substudy of the WHI, no statistically significant increase of CHD events was reported in women receiving CE/MPA compared to women receiving placebo (39 versus 33 per 10,000 women-years). An increase in relative risk was demonstrated in year 1, and a trend toward decreasing relative risk was reported in years 2 through 5 [see Clinical Studies (14.4)].

In postmenopausal women with documented heart disease (n = 2,763, average age 66.7 years), in a controlled clinical trial of secondary prevention of cardiovascular disease (Heart and Estrogen/Progestin Replacement Study [HERS]), treatment with daily CE 0.625 mg/MPA 2.5 mg demonstrated no cardiovascular benefit. During an average follow-up of 4.1 years, treatment with CE/MPA did not reduce the overall rate of CHD events in postmenopausal women with established coronary heart disease. There were more CHD events in the CE/MPA-treated group than in the placebo group in year 1, but not during the subsequent years. Two thousand, three hundred and twenty-one (2,321) women from the original HERS trial agreed to participate in an open label extension of HERS, HERS II. Average follow-up in HERS II was an additional 2.7 years, for a total of 6.8 years overall. Rates of CHD events were comparable among women in the CE/MPA group and the placebo group in HERS, HERS II, and overall.

Venous Thromboembolism (VTE)

In the estrogen alone substudy of WHI, the risk of VTE (DVT and pulmonary embolism [PE]) was reported to be increased for women receiving daily CE compared to placebo (30 versus 22 per 10,000 women-years), although only the increased risk of DVT reached statistical significance (23 versus 15 per 10,000 women-years). The increase in VTE risk was demonstrated during the first two years^3 [see Clinical Studies (14.4)].

In the estrogen plus progestin substudy of WHI, a statistically significant two-fold greater rate of VTE was reported in women receiving daily CE/MPA compared to women receiving placebo (35 versus 17 per 10,000 women-years). Statistically significant increases in risk for both DVT (26 versus 13 per 10,000 women-years) and PE (18 versus 8 per 10,000 women-years) were also demonstrated. The increase in VTE risk was observed during the first year and persisted [see Clinical Studies (14.4)].

If feasible, estrogens should be discontinued at least 4 to 6 weeks before surgery of the type associated with an increased risk of thromboembolism, or during periods of prolonged immobilization.

5.2 Malignant Neoplasms

Endometrial Cancer

An increased risk of endometrial cancer has been reported with the use of unopposed estrogen therapy in women with a uterus. The reported endometrial cancer risk among unopposed estrogen users is about 2 to 12 times greater than in nonusers, and appears dependent on duration of treatment and on estrogen dose. Most studies show no significant increased risk associated with use of estrogens for less than 1 year. The greatest risk appears associated with prolonged use, with an increased risk of 15- to 24-fold for 5 to 10 years or more. This risk has been shown to persist for at least 8 to 15 years after estrogen therapy is discontinued.

Clinical surveillance of all women using estrogen plus progestin therapy is important. Adequate diagnostic measures, including endometrial sampling when indicated, should be undertaken to rule out malignancy in all cases of undiagnosed persistent or recurring abnormal vaginal bleeding. There is no evidence that the use of natural estrogens results in a different endometrial risk profile than synthetic estrogens of equivalent estrogen dose. Adding a progestin to estrogen therapy has been shown to reduce the risk of endometrial hyperplasia, which may be a precursor to endometrial cancer.

Breast Cancer

The most important randomized clinical trial providing information about this issue in estrogen alone users is the Women's Health Initiative (WHI) substudy of daily conjugated estrogens (CE 0.625 mg). In the estrogen alone substudy of WHI, after an average of 7.1 years of follow-up, daily CE 0.625 mg was not associated with an increased risk of invasive breast cancer (relative risk [RR] 0.80, 95 percent nominal confidence interval [nCI] 0.62-1.04) [see Clinical Studies (14.4)].

The most important randomized clinical trial providing information about this issue in estrogen plus progestin users is the Women's Health Initiative (WHI) substudy of daily CE 0.625 mg plus medroxyprogesterone acetate (MPA 2.5 mg). In the estrogen plus progestin substudy, after a mean follow-up of 5.6 years, the WHI substudy reported an increased risk of breast cancer in women who took daily CE/MPA. In this substudy, prior use of estrogen alone or estrogen plus progestin therapy was reported by 26 percent of the women. The relative risk of invasive breast cancer was 1.24 (95 percent nCI 1.01-1.54), and the absolute risk was 41 versus 33 cases per 10,000 women-years, for estrogen plus progestin compared with placebo, respectively. Among women who reported prior use of hormone therapy, the relative risk of invasive breast cancer was 1.86, and the absolute risk was 46 versus 25 cases per 10,000 women-years, for estrogen plus progestin compared with placebo. Among women who reported no prior use of hormone therapy, the relative risk of invasive breast cancer was 1.09, and the absolute risk was 40 versus 36 cases per 10,000 women-years for estrogen plus progestin compared with placebo. In the same substudy, invasive breast cancers were larger and diagnosed at a more advanced stage in the CE/MPA group compared with the placebo group. Metastatic disease was rare, with no apparent difference between the two groups. Other prognostic factors, such as histologic subtype, grade and hormone receptor status did not differ between the groups [see Clinical Studies (14.4)].

Observational studies have also reported an increased risk of breast cancer for estrogen plus progestin therapy, and a smaller increased risk for estrogen alone therapy, after several years of use. The risk increased with duration of use, and appeared to return to baseline over about 5 years after stopping treatment (only the observational studies have substantial data on risk after stopping). Observational studies also suggest that the risk of breast cancer was greater, and became apparent earlier, with estrogen plus progestin therapy as compared to estrogen alone therapy. However, these studies have not found significant variation in the risk of breast cancer among different estrogens or among different estrogen plus progestin combinations, doses, or routes of administration.

The use of estrogen alone and estrogen plus progestin has been reported to result in an increase in abnormal mammograms requiring further evaluation.

All women should receive yearly breast examinations by a healthcare provider and perform monthly breast self-examinations. In addition, mammography examinations should be scheduled based on patient age, risk factors, and prior mammogram results.

Ovarian Cancer

The estrogen plus progestin substudy of the WHI reported that daily CE/MPA increased the risk of ovarian cancer. After an average follow-up of 5.6 years, the relative risk for ovarian cancer for CE/MPA versus placebo was 1.58 (95 percent nCI, 0.77-3.24) but was not statistically significant. The absolute risk for CE/MPA vs. placebo was 4.2 versus 2.7 cases per 10,000 women-years. In some epidemiologic studies, the use of estrogen-only products, in particular for 10 or more years, has been associated with an increased risk of ovarian cancer. Other epidemiologic studies have not found these associations.

5.3 Dementia

In the estrogen alone Women's Health Initiative Memory Study (WHIMS), a substudy of the WHI, a population of 2,947 hysterectomized women 65 to 79 years of age was randomized to daily conjugated estrogens (CE 0.625 mg) or placebo. In the estrogen plus progestin WHIMS substudy, a population of 4,532 postmenopausal women 65 to 79 years of age was randomized to daily CE 0.625 mg plus medroxyprogesterone acetate (MPA 2.5 mg) or placebo.

In the estrogen alone substudy, after an average follow-up of 5.2 years, 28 women in the CE alone group and 19 women in the placebo group were diagnosed with probable dementia. The relative risk of probable dementia for CE alone versus placebo was 1.49 (95 percent CI, 0.83-2.66). The absolute risk of probable dementia for CE alone versus placebo was 37 versus 25 cases per 10,000 women-years [see Use in Specific Populations (8.5) and Clinical Studies (14.5)].

In the estrogen plus progestin substudy, after an average follow-up of 4 years, 40 women in the CE/MPA group and 21 women in the placebo group were diagnosed with probable dementia. The relative risk of probable dementia for CE/MPA versus placebo was 2.05 (95 percent CI, 1.21-3.48). The absolute risk of probable dementia for CE/MPA versus placebo was 45 versus 22 cases per 10,000 women-years [see Use in Specific Populations (8.5) and Clinical Studies (14.5)].

When data from the two populations were pooled as planned in the WHIMS protocol, the reported overall relative risk for probable dementia was 1.76 (95 percent CI, 1.19-2.60). Since both substudies were conducted in women 65 to 79 years of age, it is unknown whether these findings apply to younger postmenopausal women [see Use in Specific Populations (8.5) and Clinical Studies (14.5)].

5.4 Gallbladder Disease

A two- to four-fold increase in the risk of gallbladder disease requiring surgery in postmenopausal women receiving estrogens has been reported.

5.5 Hypercalcemia

Estrogen administration may lead to severe hypercalcemia in women with breast cancer and bone metastases. If hypercalcemia occurs, use of the drug should be stopped and appropriate measures taken to reduce the serum calcium level.

5.6 Visual Abnormalities

Retinal vascular thrombosis has been reported in women receiving estrogens. Discontinue medication pending examination if there is sudden partial or complete loss of vision, or a sudden onset of proptosis, diplopia, or migraine. If examination reveals papilledema or retinal vascular lesions, estrogens should be permanently discontinued.

5.7 Addition of a Progestin When a Woman Has Not Had a Hysterectomy

Studies of the addition of a progestin for 10 or more days of a cycle of estrogen administration, or daily with estrogen in a continuous regimen, have reported a lowered incidence of endometrial hyperplasia than would be induced by estrogen treatment alone. Endometrial hyperplasia may be a precursor to endometrial cancer.

There are, however, possible risks that may be associated with the use of progestins with estrogens compared to estrogen alone regimens. These include a possible increased risk of breast cancer, adverse effects on lipoprotein metabolism (lowering HDL, raising LDL), and impairment of glucose tolerance.

5.8 Elevated Blood Pressure

In a small number of case reports, substantial increases in blood pressure have been attributed to idiosyncratic reactions to estrogens. In a large, randomized, placebo-controlled clinical trial, a generalized effect of estrogens on blood pressure was not seen. Blood pressure should be monitored at regular intervals with estrogen use.

5.9 Hypertriglyceridemia

In women with preexisting hypertriglyceridemia, estrogen therapy may be associated with elevations of plasma triglycerides leading to pancreatitis and other complications. Consider discontinuation of treatment if pancreatitis or other complications develop.

5.10 Impaired Liver Function and Past History of Cholestatic Jaundice

Estrogens may be poorly metabolized in women with impaired liver function. For women with a history of cholestatic jaundice associated with past estrogen use or with pregnancy, caution should be exercised, and in the case of recurrence, medication should be discontinued.

5.11 Hypothyroidism

Estrogen administration leads to increased thyroid-binding globulin (TBG) levels. Women with normal thyroid function can compensate for the increased TBG by making more thyroid hormone, thus maintaining free T4 and T3 serum concentrations in the normal range. Women dependent on thyroid hormone replacement therapy who are also receiving estrogens may require increased doses of their thyroid hormone replacement therapy. These women should have their thyroid function monitored in order to maintain their free thyroid hormone levels in an acceptable range.

5.12 Fluid Retention

Estrogens may cause some degree of fluid retention. Women who have conditions that might be influenced by this factor, such as a cardiac or renal dysfunction, warrant careful observation when estrogens are prescribed.

5.13 Hypocalcemia

Estrogens should be used with caution in women with preexisting severe hypocalcemia.

5.14 Exacerbation of Endometriosis

Endometriosis may be exacerbated with administration of estrogens. A few cases of malignant transformation of residual endometrial implants have been reported in women treated post-hysterectomy with estrogen alone therapy. For women known to have residual endometriosis post-hysterectomy, the addition of progestin should be considered.

5.15 Exacerbation of Other Conditions

Estrogens may cause an exacerbation of asthma, diabetes mellitus, epilepsy, migraine, porphyria, systemic lupus erythematosus and hepatic hemangiomas and should be used with caution in women with these conditions.

5.16 Alcohol-Based Products are Flammable

Avoid fire, flame or smoking until the spray has dried.

5.17 Application of Sunscreen

When sunscreen is applied approximately one hour after application of Evamist, estradiol absorption was decreased by 11 percent. When sunscreen is applied approximately one hour before the application of Evamist, no significant change in estradiol absorption was observed.

5.18 Laboratory Tests

Serum follicle stimulating hormone and estradiol levels have not been shown to be useful in the management of moderate to severe vasomotor symptoms.

5.19 Drug and Laboratory Test Interactions

Accelerated prothrombin time, partial thromboplastin time, and platelet aggregation time; increased platelet count; increased factors II, VII antigen, VIII antigen, VIII coagulant activity, IX, X, XII, VII-X complex, II-VII-X complex, and beta- thromboglobulin; decreased levels of antifactor Xa and antithrombin III, decreased antithrombin III activity; increased levels of fibrinogen and fibrinogen activity; increased plasminogen antigen and activity.

Increased TBG levels leading to increased circulating total thyroid hormone levels, as measured by protein-bound iodine (PBI), T4 levels (by column or by radioimmunoassay) or T3 levels by radioimmunoassay. T3 resin uptake is decreased, reflecting the elevated TBG. Free T4 and free T3 concentrations are unaltered. Women on thyroid hormone replacement therapy may require higher doses of thyroid hormone.

Other binding proteins may be elevated in serum (corticosteroid binding globulin [CBG], SHBG), leading to increased total circulating corticosteroids and sex steroids, respectively. Free hormone concentrations, such as testosterone and estradiol, may be decreased. As with other transdermal estradiol products, a slight increase in SHBG was seen with Evamist active drug compared with baseline.

Increased plasma HDL and HDL2 cholesterol subfraction concentrations, reduced LDL cholesterol concentration, increased triglyceride levels.

Impaired glucose tolerance.

6 ADVERSE REACTIONS

Enter section text here

6.1 Clinical Study Experience

Because clinical trials are conducted under widely varying conditions, adverse reaction rates observed in the clinical trials of a drug cannot be directly compared to rates in the clinical trials of another drug and may not reflect the rates observed in practice.

In a 12-week, randomized, placebo-controlled trial of Evamist in 454 women, 80-90 percent of women randomized to active drug received at least 70 days of therapy and 75-85 percent randomized to placebo received at least 70 days of therapy.

The adverse reactions that occurred in at least 5 percent of women in any treatment group are shown in Table 1.

Table 1. Frequency of Adverse Reactions (≥ 5%) in Any Treatment Group in a Controlled Study of Evamist
 |  | Frequency n (%)
System Organ Class Preferred Term | 1 Spray | 2 Sprays | 3 Sprays
Placebo (N = 77) | Evamist (N = 76) | Placebo (N = 76) | Evamist (N = 74) | Placebo (N = 75) | Evamist (N = 76)
Reproductive System and Breast Disorders
Breast tenderness | 0 (0) | 4 (5) | 4 (5) | 5 (7) | 0 (0) | 4 (5)
Nipple pain | 0 (0) | 2 (3) | 0 (0) | 5 (7) | 0 (0) | 1 (1)
Gastrointestinal Disorders
Nausea | 5 (7) | 1 (1) | 1 (1) | 2 (3) | 4 (5) | 2 (3)
Infections and Infestations
Nasopharyngitis | 1 (1) | 4 (5) | 2 (3) | 3 (4) | 1 (1) | 1 (1)
Musculoskeletal and Connective Tissue Disorders
Back pain | 1 (1) | 2 (3) | 2 (3) | 4 (5) | 1 (1) | 2 (3)
Arthralgia | 1 (1) | 1 (1) | 4 (5) | 1 (1) | 0 (0) | 3 (4)
Nervous system
Headache | 4 (5) | 7 (9) | 5 (7) | 9 (12) | 7 (9) | 8 (11)

Application site reactions were reported in 3 out of 226 (1.3%) women treated with Evamist.

6.2 Additional Adverse Reactions Reported With Estrogen and/or Progestin Therapy

The following additional adverse reactions have been reported with estrogen and/or progestin therapy.

Genitourinary System

Abnormal uterine bleeding/spotting, dysmenorrhea/pelvic pain, increase in size of uterine leiomyomata, vaginitis including vaginal candidiasis, change in amount of cervical secretion, changes in cervical ectropion, ovarian cancer, endometrial hyperplasia, endometrial cancer.

Breasts

Tenderness, enlargement, pain, nipple discharge, galactorrhea, fibrocystic breast changes, breast cancer.

Cardiovascular

Deep and superficial venous thrombosis, pulmonary embolism, thrombophlebitis, myocardial infarction, stroke, increase in blood pressure.

Gastrointestinal

Nausea, vomiting, abdominal cramps, bloating, cholestatic jaundice, increased incidence of gallbladder disease, pancreatitis, enlargement of hepatic hemangiomas.

Skin

Chloasma or melasma, that may persist when drug is discontinued; erythema multiforme, erythema nodosum, hemorrhagic eruption, loss of scalp hair, hirsutism, pruritus, rash.

Eyes

Retinal vascular thrombosis, intolerance to contact lenses.

Central Nervous System

Headache, migraine, dizziness, mental depression, exacerbation of chorea, nervousness, mood disturbances, irritability, exacerbation of epilepsy, dementia.

Miscellaneous

Increase or decrease in weight, glucose intolerance, aggravation of porphyria, edema, arthralgias, leg cramps, changes in libido, urticaria, angioedema, anaphylactoid/anaphylactic reactions, hypocalcemia (preexisting condition), exacerbation of asthma, increased triglycerides.

7 DRUG INTERACTIONS

No formal drug interaction studies have been conducted for Evamist.

7.1 Metabolic Interactions

In vitro and in vivo studies have shown that estrogens are metabolized partially by cytochrome P450 3A4 (CYP3A4). Therefore, inducers or inhibitors of CYP3A4 may affect estrogen drug metabolism. Inducers of CYP3A4 such as St. John's Wort preparations (Hypericum perforatum), phenobarbital, carbamazepine, and rifampin may reduce plasma concentrations of estrogens, possibly resulting in a decrease in therapeutic effects and/or changes in the uterine bleeding profile. Inhibitors of CYP3A4 such as erythromycin, clarithromycin, ketoconazole, itraconazole, ritonavir and grapefruit juice may increase plasma concentrations of estrogens and may result in side effects.

8 USE IN SPECIFIC POPULATIONS

Enter section text here

8.1 Pregnancy

Evamist should not be used during pregnancy [see Contraindications (4)]. There appears to be little or no increased risk of birth defects in children born to women who have used estrogens and progestins as an oral contraceptive inadvertently during early pregnancy.

8.3 Nursing Mothers

Evamist should not be used during lactation. Estrogen administration to nursing mothers has been shown to decrease the quantity and quality of the milk. Detectable amounts of estrogens have been identified in the milk of mothers receiving this drug.

8.4 Pediatric Use

Evamist is not intended for pediatric use and no clinical data have been collected in children.

8.5 Geriatric Use

There have not been sufficient numbers of geriatric women involved in studies utilizing Evamist to determine whether those over 65 years of age differ from younger subjects in their response to Evamist.

In the estrogen alone substudy of the Women's Health Initiative (WHI) study, 46 percent (n = 4,943) of women were 65 years of age and older, while 7.1 percent (n = 767) of women were 75 years of age and older. There was a higher relative risk (daily conjugated estrogens [CE 0.625 mg] versus placebo) of stroke in women less than 75 years of age compared to women 75 years of age and older.

In the estrogen alone substudy of the Women's Health Initiative Memory Study (WHIMS), a substudy of WHI, a population of 2,947 hysterectomized women, 65 to 79 years of age, was randomized to receive daily conjugated estrogens (CE 0.625 mg) or placebo. After an average follow-up of 5.2 years, the relative risk (CE versus placebo) of probable dementia was 1.49 (95 percent CI, 0.83-2.66). The absolute risk of developing probable dementia with estrogen alone was 37 versus 25 cases per 10,000 women-years compared to placebo.

Of the total number of women in the estrogen plus progestin substudy of WHI, 44 percent (n = 7,320) were 65 years of age and older, while 6.6 percent (n = 1,095) were 75 years of age and older. In women 75 years of age and older compared to women less than 75 years of age, there was a higher relative risk of non-fatal stroke and invasive breast cancer in the estrogen plus progestin group versus placebo. In women greater than 75 years of age, the increased risk of non-fatal stroke and invasive breast cancer observed in the estrogen plus progestin group compared to placebo was 75 versus 24 per 10,000 women-years and 52 versus 12 per 10,000 women-years, respectively.

In the estrogen plus progestin WHIMS substudy, a population of 4,532 postmenopausal women, 65 to 79 years of age, was randomized to receive daily CE 0.625 mg/MPA 2.5 mg or placebo. In the estrogen plus progestin group, after an average follow-up of 4 years, the relative risk (CE/MPA versus placebo) of probable dementia was 2.05 (95 percent CI, 1.21-3.48). The absolute risk of developing probable dementia with CE/MPA was 45 versus 22 cases per 10,000 women-years compared to placebo.

Seventy-nine (79) percent of the cases of probable dementia occurred in women that were older than 70 for the CE alone group, and 82 percent of the cases of probable dementia occurred in women who were older than 70 in the CE/MPA group. The most common classification of probable dementia in both the treatment groups and placebo groups was Alzheimer's disease.

When data from the two populations were pooled as planned in the WHIMS protocol, the reported overall relative risk for probable dementia was 1.76 (95 percent CI, 1.19-2.60). Since both substudies were conducted in women 65 to 79 years of age, it is unknown whether these findings apply to younger postmenopausal women [see Warnings and Precautions (5.3)].

10 OVERDOSAGE

Overdosage of estrogen may cause nausea and vomiting, breast tenderness, dizziness, abdominal pain, drowsiness/fatigue and withdrawal bleeding may occur in women. Treatment of overdose consists of discontinuation of Evamist together with institution of appropriate symptomatic care.

11 DESCRIPTION

Evamist (estradiol transdermal spray) is designed to deliver estradiol to the blood circulation following topical application to the skin of a rapidly drying solution from a metered-dose pump.

Evamist is a homogeneous solution of 1.7% estradiol USP (active ingredient) in alcohol USP and octisalate USP formulated to provide sustained release of the active ingredient into the systemic circulation.

Estradiol USP is a white crystalline powder, chemically described as estra-1,3,5(10)-triene-3,17β-diol. It has an empirical formula of C18H24O2·1/2 H2O and molecular weight of 281.4. The structural formula is:

Each metered-dose pump contains 8.1 mL and is designed to accurately deliver 75 sprays of 90 mcL each after priming. One spray of Evamist contains 1.53 mg estradiol. The metered-dose pump should be held upright and vertical for spraying. Before a new applicator is used for the first time, the pump should be primed by spraying 3 times into the cover.

One, two or three sprays are applied daily to adjacent non-overlapping 20 cm^2 areas on the inner surface of the arm between the elbow and the wrist and allowed to dry.

12 CLINICAL PHARMACOLOGY

Enter section text here

12.1 Mechanism of Action

Endogenous estrogens are largely responsible for the development and maintenance of the female reproductive system and secondary sexual characteristics. Although circulating estrogens exist in a dynamic equilibrium of metabolic interconversions, estradiol is the principal intracellular human estrogen and is substantially more potent than its metabolites, estrone and estriol, at the receptor level.

The primary source of estrogen in normally cycling adult women is the ovarian follicle, which secretes 70 to 500 mcg of estradiol daily, depending on the phase of the menstrual cycle. After menopause, most endogenous estrogen is produced by conversion of androstenedione, secreted by the adrenal cortex, to estrone by peripheral tissues. Thus, estrone and the sulfate conjugated form, estrone sulfate, are the most abundant circulating estrogens in postmenopausal women.

12.2 Pharmacodynamics

Estrogens act through binding to nuclear receptors in estrogen-responsive tissues. To date, two estrogen receptors have been identified. These vary in proportions from tissue to tissue.

Circulating estrogens modulate the pituitary secretion of the gonadotropins, luteinizing hormone (LH) and follicle stimulating hormone (FSH), through a negative feedback mechanism. Estrogens act to reduce the elevated levels of these hormones seen in postmenopausal women.

12.3 Pharmacokinetics

Absorption

In a multiple-dose study, 72 postmenopausal women were treated for 14 days with Evamist to the inner forearm. Serum concentrations of estradiol appeared to reach steady state after 7 to 8 days of application of one, two, or three 90-mcL sprays of Evamist per day (Figure 1).

Figure 1. Mean (±SD) Serum Estradiol Concentrations on Day 14 Following Topical Application for 14 Days of One, Two or Three Sprays of Evamist (Unadjusted for Baseline)

Pharmacokinetics parameters for estradiol from one, two, or three 90-mcL sprays of Evamist, as assessed on Day 14 of this study, are described in Table 2.

Table 2. Estradiol Pharmacokinetic Parameters on Day 14 (Unadjusted for Baseline)
PK Parameter | Number of Daily Sprays of Evamist
1 Spray (N = 24) | 2 Spray (N = 23) | 3 Spray (N = 24)
Cmax (pg/mL)^1 Cmin (pg/mL)^1 Cavg (pg/mL)^1 AUC0-24 (pg*hr/mL)^1 Tmax (hours)^2 | 36.4 (62) 11.3 (52) 19.6 (49) 471 (49) 20 (0-24) | 57.4 (94) 18.1 (51) 30.7 (43) 736 (43) 18 (0-24) | 54.1 (50) 19.6 (27) 30.9 (30) 742 (30) 20 (0-24)

^1 Values expressed are arithmetic means (%CV)
^2 Values expressed are medians (minimum-maximum)

Distribution

The distribution of exogenous estrogens is similar to that of endogenous estrogens. Estrogens are widely distributed in the body and are generally found in higher concentrations in the sex hormone target organs. Estrogens circulate in blood largely bound to sex hormone binding globulin (SHBG) and albumin.

Metabolism

Exogenous estrogens are metabolized in the same manner as endogenous estrogens. Circulating estrogens exist in a dynamic equilibrium of metabolic interconversions. These transformations take place mainly in the liver. Estradiol is converted reversibly to estrone, and both can be converted to estriol, which is a major urinary metabolite. Estrogens also undergo enterohepatic recirculation via sulfate and glucuronide conjugation in the liver, biliary secretion of conjugates into the intestine, and hydrolysis in the intestine followed by reabsorption. In postmenopausal women, a significant proportion of the circulating estrogens exist as sulfate conjugates, especially estrone sulfate, which serves as a circulating reservoir for the formation of more active estrogens.

Excretion

Estradiol, estrone and estriol are excreted in the urine along with glucuronide and sulfate conjugates.

13 NONCLINICAL TOXICOLOGY

Enter section text here

13.1 Carcinogenesis, Mutagenesis, Impairment of Fertility

Long-term continuous administration of natural and synthetic estrogens in certain animal species increases the frequency of carcinomas of the breast, uterus, cervix, vagina, testis and liver.

14 CLINICAL STUDIES

Enter section text here

14.1 Effects on Vasomotor Symptoms

In a 12-week, randomized, double-blind, placebo-controlled clinical trial, a total of 454 postmenopausal women (average 53 years of age, 70 percent Caucasian and 24 percent African-American) were randomized and received at least one dose of Evamist (one, two or three 90-mcL sprays) or placebo. Generally healthy postmenopausal women were enrolled with a mean total frequency of greater than or equal to 56 moderate to severe vasomotor symptoms per week (greater than or equal to 8 per day).

Efficacy was determined as a statistically significant and clinically significant (at least two per day or 14 per week difference) reduction in hot flush frequency and a statistically significant reduction in severity for Evamist versus placebo. One, two or three daily sprays of Evamist were shown to be better than placebo for relief of frequency (Table 3) and severity (Table 4) of moderate to severe vasomotor symptoms at Week 4 and Week 12.

Table 3. Effect of Treatment on the Daily Frequency of Moderate to Severe Vasomotor Symptoms at Week 4 and Week 12 (Intent-To-Treat Population, LOCF)
 |  | Mean Change from Baselinea (SD)
Treatment (N) | Baseline Mean (SD) | Week 4 Mean (SD) | Week 12 Mean (SD)
1 Spray
Evamist (N=76) | 11.81 (4.07) | -6.26 (4.01) | -8.10 (4.02)
Placebo (N=77) | 12.41 (5.59) | -3.64 (5.30) | -4.76 (5.84)
Differenceb | — | -2.62 | -3.34
p-valuec | — | 0.0010 | 0.0004
2 Sprays
Evamist (N=74) | 12.66 (7.33) | -7.30 (6.93) | -8.66 (6.65)
Placebo (N=76) | 12.13 (6.10) | -4.74 (4.38) | -6.19 (5.77)
Differenceb | — | -2.56 | -2.47
p-valuec | — | 0.0027 | 0.0099
3 Sprays
Evamist (N=76) | 10.78 (3.58) | -6.64 (4.23) | -8.44 (4.50)
Placebo (N=75) | 12.55 (11.94) | -4.54 (7.40) | -5.32 (6.30)
Differenceb | — | -2.10 | -3.12
p-valuec | — | 0.0002 | less than 0.0001

a Mean change and difference based on raw data
b Evamist versus placebo
c Tests for pairwise differences using ANCOVA

Table 4. Effect of Treatment on the Weekly Severity of Moderate to Severe Vasomotor Symptoms at Week 4 and Week 12 (Intent-To-Treat Population, LOCF) a
 |  | Mean Change from Baselineb (SD)
Treatment (N) | Baseline Mean (SD) | Week 4 Mean (SD) | Week 12 Mean (SD)
1 Spray
Evamist (N=76) | 2.53 (0.25) | -0.47 (0.80) | -1.04 (1.01)
Placebo (N=77) | 2.55 (0.25) | -0.19 (0.55) | -0.26 (0.60)
Differencec | — | -0.28 | -0.78
p-valued | — | 0.0573 | less than 0.0001
2 Sprays
Evamist (N=74) | 2.54 (0.21) | -0.57 (0.83) | -0.92 (1.01)
Placebo (N=76) | 2.54 (0.22) | -0.25 (0.64) | -0.54 (0.89)
Differencec | — | -0.32 | -0.38
p-valued | — | 0.0160 | 0.0406
3 Sprays
Evamist (N=76) | 2.58 (0.25) | -0.43 (0.66) | -1.07 (1.01)
Placebo (N=75) | 2.54 (0.24) | -0.13 (0.53) | -0.31 (0.75)
Differencec | — | -0.30 | -0.76
p-valued | — | 0.0031 | less than 0.0001

a Severity score calculated as: (2 x number moderate +3 x number severe)/ number moderate + number severe)
b Mean chane and difference based on raw data
c Evamist versus placebo
d Tests for pairwise differences using ANCOVA

14.2 Effect of Application Site Washing

Site washing one hour after the application of three 90-mcL sprays to the inner forearm did not have a significant effect on average 24-hour serum concentrations of estradiol.

14.3 Potential for Estradiol Transfer

The effect of estradiol transfer was evaluated in 20 healthy postmenopausal women who applied three 90-mcL sprays of Evamist to the inner forearm once daily. One hour after applying Evamist, subjects held the dosed forearm against the inner forearm of a non-dosed (recipient) male subject for one 5-minute period of continual contact. No significant transfer of estradiol was observed in persons who came in contact with the application site of estradiol-treated individuals.

14.4 Women's Health Initiative Studies

The Women's Health Initiative (WHI) enrolled approximately 27,000 predominantly healthy postmenopausal women in two substudies to assess the risks and benefits of either the use of daily oral conjugated estrogens (CE 0.625 mg) alone or in combination with medroxyprogesterone acetate (MPA 2.5 mg) compared to placebo in the prevention of certain chronic diseases. The primary endpoint was the incidence of coronary heart disease (CHD) (nonfatal myocardial infarction [MI], silent MI and CHD death), with invasive breast cancer as the primary adverse outcome studied. A “global index” included the earliest occurrence of CHD, invasive breast cancer, stroke, pulmonary embolism (PE), endometrial cancer (only in the CE/MPA substudy), colorectal cancer, hip fracture, or death due to other cause. These substudies did not evaluate the effects of CE or CE/MPA on menopausal symptoms.

The estrogen alone substudy was stopped early because an increased risk of stroke was observed, and it was deemed that no further information would be obtained regarding the risks and benefits of estrogen alone in predetermined primary endpoints. Results of the estrogen alone substudy, which included 10,739 women (average 63 years of age, range 50 to 79 years of age; 75.3 percent White, 15.1 percent Black, 6.1 percent Hispanic, 3.6 percent Other), after an average follow-up of 6.8 years are presented in Table 5.

For those outcomes included in the WHI “global index” that reached statistical significance, the absolute excess risk per 10,000 women-years in the group treated with CE alone was 12 more strokes, while the absolute risk reduction per 10,000 women-years was 6 fewer hip fractures. The absolute excess risk of events included in the “global index” was a non-significant 2 events per 10,000 women-years. There was no difference between the groups in terms of all-cause mortality [see Warnings and Precautions (5)].

Final centrally adjudicated results for CHD events and centrally adjudicated results for invasive breast cancer incidence from the estrogen alone substudy, after an average follow-up of 7.1 years, reported no overall difference for primary CHD events (nonfatal MI, silent MI and CHD death) and invasive breast cancer incidence in women receiving CE alone compared to placebo (see Table 5).^2,4

Centrally adjudicated results for stroke events from the estrogen alone substudy, after an average follow-up of 7.1 years, reported no significant differences in distribution of stroke subtypes or severity, including fatal strokes, in women receiving CE alone compared to placebo. Estrogen alone increased the risk for ischemic stroke, and this excess risk was present in all subgroups of women examined (see Table 5).^1

The estrogen plus progestin substudy was also stopped early. According to the predefined stopping rule, after an average follow-up of 5.2 years of treatment, the increased risk of breast cancer and cardiovascular events exceeded the specified benefits included in the “global index.” The absolute excess risk of events included in the “global index” was 19 per 10,000 women-years (relative risk [RR] 1.15, 95 percent nCI, 1.03-1.28).

For those outcomes included in the WHI “global index” that reached statistical significance after 5.6 years of follow-up, the absolute excess risks per 10,000 women-years in the group treated with CE/MPA were 6 more CHD events, 7 more strokes, 10 more PEs, and 8 more invasive breast cancers, while the absolute risk reduction per 10,000 women-years were 7 fewer colorectal cancers and 5 fewer hip fractures [see Warnings and Precautions (5)].

Results of the estrogen plus progestin substudy, which included 16,608 women (average 63 years of age, range 50 to 79 years of age; 83.9 percent White, 6.5 percent Black, 5.4 percent Hispanic, 3.9 percent Other) are presented in Table 6. These results reflect centrally adjudicated data after an average follow-up of 5.6 years.

Table 5. Relative and Absolute Risk Seen in the Estrogen Alone Substudy of WHI
Event | Relative Risk CE vs. Placebo (95% nCIa) | Placebo (n = 5,429) | CE (n = 5,310)
Absolute Risk per 10,000 Women-Years
CHD eventsb Non-fatal MIb CHD deathb | 0.95 (0.79-1.16) 0.91 (0.73-1.14) 1.01 (0.71-1.43) | 56 43 16 | 53 40 16
Strokeb Ischemicb | 1.37 (1.09-1.73) 1.55 (1.19-2.01) | 33 25 | 45 38
Deep vein thrombosisb,d | 1.47 (1.06-2.06) | 15 | 23
Pulmonary embolismb | 1.37 (0.90-2.07) | 10 | 14
Invasive breast cancerb | 0.80 (0.62-1.04) | 34 | 28
Colorectal cancerc | 1.08 (0.75-1.55) | 16 | 17
Hip fracturec | 0.61 (0.41-0.91) | 17 | 11
Vertebral fracturesc,d | 0.62 (0.42-0.93) | 17 | 11
Total fracturesc,d | 0.70 (0.63-0.79) | 195 | 139
Death due to other causes | 1.08 (0.88-1.32) | 50 | 53
Overall mortalityc,d | 1.04 (0.88-1.22) | 78 | 81
Global indexc,f | 1.01 (0.91-1.12) | 190 | 192

a Nominal confidence intervals unadjusted for multiple looks and multiple comparisons.
b Results are based on centrally adjudicated data for an average follow-up of 7.1 years.
c Results are based on an average follow-up of 6.8 years.
d Not included in global index.
e All deaths, except from breast or colorectal cancer, definite/probable CHD, PE or cerebrovascular disease.
f A subset of the events was combined in a “global index,” defined as the earliest occurrence of CHD events, invasive breast cancer, stroke, pulmonary embolism, endometrial cancer, colorectal cancer, hip fracture, or death due to other causes.

14.5 Women's Health Initiative Memory Study

The estrogen alone Women's Health Initiative Memory Study (WHIMS), a substudy of theWHI, enrolled 2,947 predominantly healthy postmenopausal women 65 years of age and older (45 percent were 65 to 69 years of age, 36 percent were 70 to 74 years of age, and 19 percent were 75 years of age and older) to evaluate the effects of daily conjugated estrogen (CE 0.625 mg) on the incidence of probable dementia (primary outcome) compared to placebo.

After an average follow-up of 5.2 years, 28 women in the estrogen alone group (37 per 10,000 women-years) and 19 in the placebo group (25 per 10,000 women-years) were diagnosed with probable dementia. The relative risk of probable dementia in the estrogen alone group was 1.49 (95 percent CI, 0.83-2.66) compared to placebo. It is unknown whether these findings apply to younger postmenopausal women [see Warnings and Precautions (5.3) and Use in Specific Populations (8.5)].

The estrogen plus progestin WHIMS substudy enrolled 4,532 predominantly healthy postmenopausal women 65 years of age and older (47 percent were 65 to 69 years of age, 35 percent were 70 to 74 years of age, and 18 percent were 75 years of age and older) to evaluate the effects of daily CE 0.625 mg plus medroxyprogesterone acetate (MPA 2.5 mg) on the incidence of probable dementia (primary outcome) compared to placebo.

After an average follow-up of 4 years, 40 women in the estrogen plus progestin group (45 per 10,000 women-years) and 21 in the placebo group (22 per 10,000 women-years) were diagnosed with probable dementia. The relative risk of probable dementia in the hormone therapy group was 2.05 (95 percent CI, 1.21- 3.48) compared to placebo.

When data from the two populations were pooled as planned in the WHIMS protocol, the reported overall relative risk for probable dementia was 1.76 (95 percent CI, 1.19-2.60). Differences between groups became apparent in the first year of treatment. It is unknown whether these findings apply to younger postmenopausal women [see Warnings and Precautions (5.3) and Use in Specific Populations (8.5)].

Table 6. Relative and Absolute Risk Seen in the Estrogen Plus Progestin Substudy of WHI at an Average of 5.6 Yearsa
Event | Relative Risk CE/MPA vs. Placebo (95% nCIb) | Placebo (n = 8,102) | CE/MPA (n = 8,506)
Absolute Risk per 10,000 Women-Years
CHD events Non-fatal MI CHD death | 1.24 (1.00-1.54) 1.28 (1.00-1.63) 1.10 (0.70-1.75) | 33 25 8 | 39 31 8
All strokes Ischemic stroke | 1.31 (1.02-1.68) 1.44 (1.09-1.90) | 24 18 | 31 26
Deep vein thrombosis | 1.95 (1.43-2.67) | 13 | 26
Pulmonary embolism | 2.13 (1.45-3.11) | 8 | 18
Invasive breast cancerc | 1.24 (1.01-1.54) | 33 | 41
Invasive colorectal cancer | 0.56 (0.38-0.81) | 16 | 9
Endometrial cancer | 0.81 (0.48-1.36) | 7 | 6
Cervical cancer | 1.44 (0.47-4.42) | 1 | 2
Hip fracture | 0.67 (0.47-0.96) | 16 | 11
Vertebral fractures | 0.65 (0.46-0.92) | 17 | 11
Lower arm/wrist fractures | 0.71 (0.59-0.85) | 62 | 44
Total fractures | 0.76 (0.69-0.83) | 199 | 152

a Results are based on centrally adjudicated data. Mortality data was not part of the adjudicated data; however, data at 5.2 years of follow-up showed no difference between the groups in terms of all-cause mortality (RR 0.98, 95 percent nCI, 0.82-1.18).

b Nominal confidence intervals unadjusted for multiple looks and multiple comparisons.
c Includes metastatic and non-metastatic breast cancer, with the exception of in situ breast cancer.

15 REFERENCES

1. Hendrix, SL, et al. Effects of conjugated equine estrogen on stroke in the Women's Health Initiative. Circulation. 2006;113:2425-2434.
2. Hsia J, et al. Conjugated equine estrogens and coronary heart disease. Arch Int Med. 2006;166:357–365.
3. Curb JD, et al. Venous thrombosis and conjugated equine estrogen in women without a uterus. Arch Int Med. 2006; 166:772-780.
4. Stefanick ML, et al. Effects of conjugated equine estrogens on breast cancer and mammography

16 HOW SUPPLIED/STORAGE AND HANDLING

Evamist (NDC 54868-6157-0) is supplied as a homogeneous solution of estradiol USP, octisalate USP and alcohol USP. The liquid formulation of Evamist is packaged in a glass vial fitted with a metered-dose pump. The unit is encased in a plastic housing with a conical bell opening that controls the distance, angle, and area of application of the metered-dose spray. Each metered-dose pump contains 8.1 mL and is designed to accurately deliver 75 sprays of 90 mcL after priming. One spray contains 1.53 mg estradiol.

Keep out of reach of children.

Alcohol and alcohol-based liquids are flammable. Avoid fire, flame or smoking until the spray has dried

Store at 25°C (77°F) with excursion permitted to 15° to 30°C (59° to 86°F). Do not freeze.

17 PATIENT COUNSELING INFORMATION

See FDA-Approved Patient Labeling (17.3)

17.1 Vaginal Bleeding

Inform women of the importance of reporting vaginal bleeding to their healthcare provider as soon as possible.

17.2 Common Adverse Reactions with Estrogen

Inform women of the possible side effects of estrogen therapy such as headache, breast pain and tenderness, nausea and vomiting.

17.3 FDA-Approved Patient Labeling

Evamist
(estradiol transdermal spray)

Instructions for use.
Read carefully.

Read this PATIENT INFORMATION before you start using Evamist and read the patient information each time you refill your Evamist prescription. There may be new information. This information does not take the place of talking to your healthcare provider about your menopausal symptoms and their treatment.

WHAT IS THE MOST IMPORTANT INFORMATION I SHOULD KNOW ABOUT EVAMIST (AN ESTROGEN HORMONE)?

- Estrogens increase the chance of getting cancer of the uterus.
  Report any unusual vaginal bleeding right away while you are using Evamist. Vaginal bleeding after menopause may be a warning sign of cancer of the uterus (womb). Your healthcare provider should check any unusual vaginal bleeding to find out the cause.
- Do not use estrogens with or without progestins to prevent heart disease, heart attacks, strokes or dementia.
  Using estrogens, with or without progestins, may increase your chance of getting heart attacks, strokes, breast cancer, and blood clots. Using estrogen, with or without progestins, may increase your chance of getting dementia, based on a study of women 65 years of age or older. You and your healthcare provider should talk regularly about whether you still need treatment with Evamist.

What is Evamist?

Evamist is a medicine that contains estradiol (an estrogen hormone). When applied to the skin, estradiol is absorbed through the skin into the bloodstream.

What is Evamist used for?

Evamist is used after menopause to:

- Reduce moderate to severe hot flashes

Estrogens are hormones made by a woman's ovaries. The ovaries normally stop making estrogens when a woman is between 45 and 55 years old. This drop in body estrogen levels causes the “change of life” or menopause (the end of monthly menstrual periods). Sometimes, a woman's ovaries are removed during an operation that causes “surgical menopause.”

When the estrogen levels begin dropping, some women get very uncomfortable symptoms, such as feelings of warmth in the face, neck, and chest, or sudden strong feelings of heat and sweating (“hot flashes” or “hot flushes”). In some women, the symptoms are mild, and they will not need estrogen treatment. In other women, symptoms can be more severe. You and your healthcare provider should talk regularly about whether you still need treatment with Evamist.

Who should not use Evamist?

Do not start using Evamist if you:

- Have unusual vaginal bleeding
- Currently have or have had certain cancers

Estrogens may increase the chance of getting certain types of cancers, including cancer of the breast or uterus. If you have or have had cancer, talk with your healthcare provider about whether you should use Evamist.

- Had a stroke or heart attack in the past year
- Currently have or have had blood clots
- Currently have or have had liver problems
- Are allergic to any of the ingredients in Evamist

See the list of ingredients in Evamist at the end of this leaflet

- Think you may be pregnant

Tell your healthcare provider:

- If you are breastfeeding

The hormone in Evamist can pass into your breast milk.

- About all your medical problems

Your healthcare provider may need to check you more carefully if you have certain conditions, such as asthma (wheezing), epilepsy (seizures), migraine, endometriosis, lupus, or problems with your heart, liver, thyroid, kidneys, or have high calcium levels in your blood.

- About all the medicines you take

This includes prescription and nonprescription medicines, vitamins, and herbal supplements. Some medicines may affect how Evamist works. Evamist may also affect how your other medicines work.

- If you are going to have surgery or will be on bed rest

You may need to stop taking estrogens.

How should I use Evamist?

Evamist is available in a spray applicator that delivers a measured amount of estradiol to the skin with each spray (see Illustration 1).

Illustration 1

It is important that you read and follow these directions on how to use Evamist properly.

- Before using the applicator for the first time, it must be primed. With the cover on, and the applicator upright, fully depress the applicator three times with your thumb or index finger. This is called priming (see Illustration 2). After priming, the applicator is ready to use. The applicator should be primed only once when you first start using a new applicator. DO NOT PRIME THE APPLICATOR BEFORE EACH DAY'S DOSE.

Illustration 2

- Apply Evamist at the same time each day.
- Apply your daily dose of Evamist to clean, dry, unbroken skin on the inside of the forearm between the elbow and the wrist (see Illustration 3). Do not apply Evamist to other areas of the skin. To apply the dose, remove the plastic cover, hold the applicator upright and rest the plastic cone flat against the skin. You may need to change the position of your arm or the position of the cone on your arm so that the cone is flat against your skin and there are no gaps between the cone and your skin. Depress the pump fully once.

Illustration 3

- If your healthcare provider tells you to increase the dose to 2 or 3 sprays, you should move the cone before applying the second or third spray to an area of the skin next to but not touching the area of the previous spray (see Illustration 4).

Illustration 4

- Always place the protective cover back on the cone of the applicator.
- Do not massage or rub Evamist into the skin. Simply allow the spray to dry for at least 2 minutes before dressing, and at least 30 minutes before washing.
- Evamist contains alcohol, and alcohol-based liquids are flammable. Avoid fire, flame or smoking when using Evamist until the spray has dried. Do not apply Evamist while standing near a flame.
- Never apply Evamist directly to the breast or in or around the vagina.

Start at the lowest dose (1 spray) and talk to your healthcare provider about how well that dose is working for you. Treatment with estrogen should be started at the lowest dose possible, and used only for as long as needed to provide relief of moderate to severe hot flashes associated with menopause. You and your healthcare provider should talk regularly (every 3-6 months) about the dose you are taking and whether you still need treatment with Evamist.

The Evamist applicator contains enough product to allow for initial priming of the pump with three sprays plus application for 75 sprays. The product will last approximately 75 days if you use 1 spray each day, 37 days if you use 2 sprays each day and 25 days if you use 3 sprays each day.

Do not use this applicator for more than 75 sprays even though the bottle may not be completely empty.

Evamist can be stored in a clean, dry place at room temperature (15° to 30°C or 59° to 86°F) and does not need refrigeration. Do not freeze. Evamist should not be used after the expiration date. When the applicator has been used for 75 sprays you can discard it in normal household waste.

What should I do if I miss a dose?

If you miss a dose, do not double the dose on the next day to catch up. If your next dose is less than 12 hours away, it is best just to wait and apply your normal dose the next day. If it is more than 12 hours until the next dose, apply the dose you missed and resume your normal dosing the next day.

What should I avoid while using Evamist?

- Do not allow others to make contact with the area of skin where you applied the spray for at least 30 minutes after application.
- Evamist contains alcohol and alcohol-based liquids are flammable. Avoid fire, flame or smoking until the spray has dried.

What are the possible side effects of estrogens?

Side effects are grouped by how serious they are and how often they happen when you are treated.

Serious but less common side effects include:

- Breast cancer
- Cancer of the uterus
- Stroke
- Heart attack
- Blood clots
- Dementia
- Gallbladder disease
- Ovarian cancer
- High blood pressure
- Liver problems
- High blood sugar
- Enlargement of benign tumors of the uterus (“fibroids”)

Some of the warning signs of these serious side effects include:

- Breast lumps
- Unusual vaginal bleeding
- Dizziness and faintness
- Changes in speech
- Severe headaches
- Chest pain
- Shortness of breath
- Pains in your legs
- Changes in vision
- Vomiting
- Yellowing of the skin, eyes or nail beds

Call your healthcare provider right away if you get any of these warning signs, or any other unusual symptoms that concern you.

Less serious but common side effects include:

- Headache
- Breast pain
- Irregular vaginal bleeding or spotting
- Stomach/abdominal cramps, bloating
- Nausea and vomiting
- Hair loss
- Fluid retention
- Vaginal yeast infection

These are not all of the possible side effects of Evamist. For more information, ask your healthcare provider or pharmacist.

What can I do to lower my chances of a serious side effect with Evamist?

- Talk with your healthcare provider regularly about whether you should continue using Evamist.
- If you have a uterus, talk with your healthcare provider about whether the addition of a progestin (a different prescribed hormone medication) is right for you. The addition of a progestin is generally recommended for women with a uterus to reduce the chance of getting cancer of the uterus.
- See your healthcare provider right away if you get vaginal bleeding while using Evamist.
- Have a pelvic exam, breast exam, and mammogram (breast X-ray) every year unless your healthcare provider tells you otherwise. If members of your family have had breast cancer or if you have had breast lumps or an abnormal mammogram, you may need to have breast exams more often.
- If you have high blood pressure, high cholesterol (fat in the blood), diabetes, are overweight, or if you use tobacco, you may have a higher chance of getting heart disease. Ask your healthcare provider for ways to lower your chances of getting heart disease.

General information about the safe and effective use of Evamist.

Medicines are sometimes prescribed for conditions that are not mentioned in patient information leaflets. Do not use Evamist for conditions for which it was not prescribed. Do not give Evamist to other people, even if they have the same symptoms you have. It may harm them.

Keep Evamist out of the reach of children.

This leaflet provides a summary of the most important information about Evamist. If you would like more information, talk with your healthcare provider or pharmacist. You can ask for information about Evamist that is written for health professionals.

You can get more information by calling the toll free number (877) 567-7676.

What are the ingredients in Evamist?

Active ingredient: estradiol (an estrogen hormone)

Inactive ingredients: octisalate (a common active ingredient in some sunscreens used to enhance skin penetration), alcohol (to dissolve the drug)

Manufactured by
DPT
San Antonio, TX 78215

for
Ther-Rx Corporation
St. Louis, MO 63044

Relabeling of "Additional Barcode Label" by:
Physicians Total Care, Inc.
Tulsa, OK 74146

Evamist (estradiol transdermal spray) Applicator

Evamist

(estradiol transdermal spray)

For Topical Use Only

Metered-dose pump delivers
75 sprays. Each spray
contains 1.53 mg of estradiol.

See Patient Leaflet for
dosing information.

Important: Applicator
not child resistant.
Keep out of the reach of children.

Flammable: Avoid
fire, flame, or smoking during use.

Store at room temperature
15° to 30°C(59° to 86°F).

Do not freeze.

Rx Only 0.27 fl oz. (8.1 mL)

Marketed by Ther-Rx Corporation
St. Louis, Mo 63044 P6000 07/09

Evamist (estradiol transdermal spray) Applicator Dust Cover

Evamist

(estradiol transdermal spray)

P6004 07/09

PRINCIPAL DISPLAY PANEL

Evamist

(estradiol transdermal spray)

One spray contains 1.53 mg of estradiol

0.27 fl oz. (8.1 mL)

Rx Only